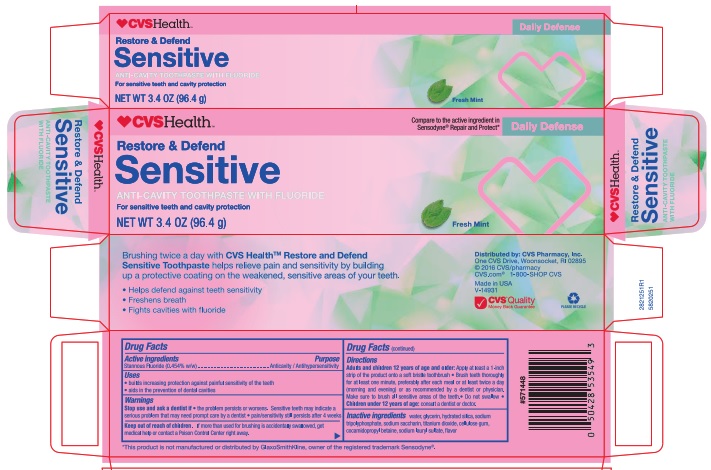 DRUG LABEL: CVS Pharmacy
NDC: 69842-251 | Form: PASTE, DENTIFRICE
Manufacturer: CVS Pharmacy
Category: otc | Type: HUMAN OTC DRUG LABEL
Date: 20251114

ACTIVE INGREDIENTS: STANNOUS FLUORIDE 0.15 g/100 g
INACTIVE INGREDIENTS: SACCHARIN SODIUM; GLYCERIN; WATER; SODIUM TRIPOLYPHOSPHATE; TITANIUM DIOXIDE; CARBOXYMETHYLCELLULOSE SODIUM; HYDRATED SILICA; COCAMIDOPROPYL BETAINE; SODIUM LAURYL SULFATE

5820251 CVS Restore & Defend Sensitive Fresh Mint

Active ingredient

Stannous Fluoride (0.454% w/w)

Purpose

Anticavity/Antihypersensitivity

Uses

- builds increasing protection against painful sensitivity of the teeth
- aids in the prevention of dental cavities

Warnings

Stop use and ask a dentist if

- the problem persists or worsens. Sensitive teeth may indicate a serious problem that may need prompt care by a dentist
- pain / sensitivity still persists after 4 weeks

Keep out of reach of children. If more than used for brushing is accidently swallowed, get medical help or contact a Poison Control Center right away.

Directions

Adults and children 12 years of age and older: Apply at least a 1-inch strip of the product onto a soft bristle toothbrush.

- Brush teeth thoroughly for at least one minute, preferably after each meal or at least twice a day (morning and evening) or as recommended by a dentist or physician. Make sure to brush all sensitive areas of the teeth
- Do not swallow

- Children under 12 years of age: consult a dentist or doctor

INACTIVE INGREDIENT

Inactive ingredients water, glycerin, hydrated silica, sodium tripolyphosphate, sodium saccharin, titanium dioxide, cellulose gum, cocamidopropyl betaine, sodium lauryl sulfate, flavor